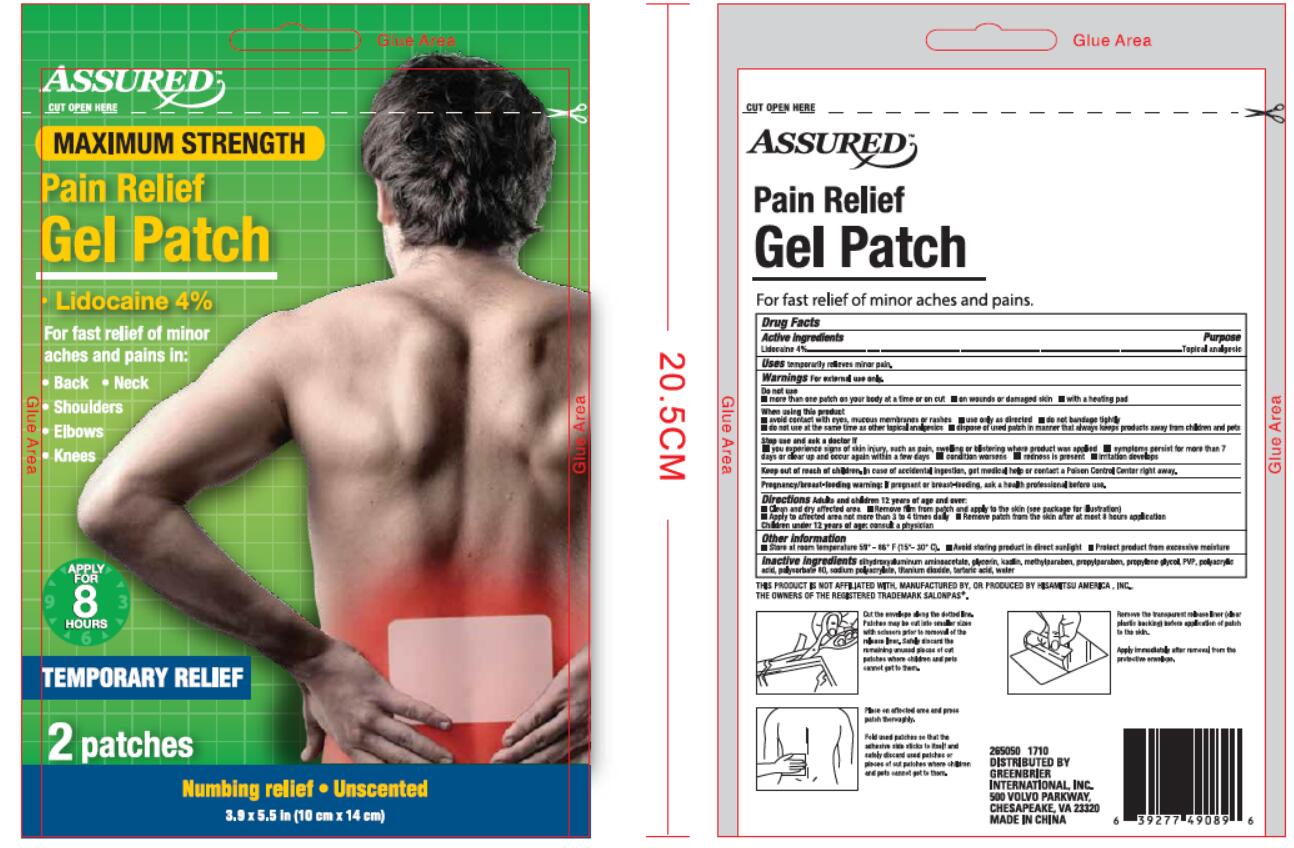 DRUG LABEL: Assured Pain Relief
NDC: 69159-101 | Form: KIT | Route: TOPICAL
Manufacturer: Foshan Aqua Gel Biotech Co., Ltd.,
Category: otc | Type: HUMAN OTC DRUG LABEL
Date: 20170910

ACTIVE INGREDIENTS: LIDOCAINE 4 g/100 g
INACTIVE INGREDIENTS: DIHYDROXYALUMINUM AMINOACETATE; GLYCERIN; KAOLIN; METHYLPARABEN; PROPYLPARABEN; PROPYLENE GLYCOL; POVIDONE, UNSPECIFIED; POLYACRYLIC ACID (8000 MW); POLYSORBATE 80; SODIUM POLYACRYLATE (8000 MW); TITANIUM DIOXIDE; TARTARIC ACID; WATER

Drug Facts

Active ingredients

Lidocaine 4%

Purpose

Topical analgesic

INDICATIONS AND USAGE

Uses temporarily releives minor pain

Warnings for external use only.

Do not use

•more than one patch on your body at a time or on cut •on wounds or damaged skin •with a heating pad

When using this product

•avoid contact with eyes, mucous membranes or rashes •use only as directed •do not bandage tightly

•do not use at the same time as other topical analgesics •dispose of used patch in a manner that always keeps products away from children and pets

Stop use and ask a doctor if

•you experience signs of skin injury, such as pain, swelling or blistering where product was applied •symptoms persist for more than 7

days or clear up and occur again within a few days •condition worsens •redness is present •irritation develops

Keep out of reach of children. On case of accidental ingestion, get medical help or contact a Poison Control Center right away.

PREGNANCY OR BREAST FEEDING

Pregnancy.breast-feeding warning. If pregant or breast-feeding, ask a health professional before use.

DOSAGE AND ADMINISTRATION

Directions Adults and children 12 years of age and over:

•Clean and dry affected area •Remove film from patch and apply to the skin (see package for instructions)

•Apply to affected area not more than 3 to 4 times daily •Remove patch from the skin after at most 8 hours of application

Children under 12 years of age: consult a physician

Other information

•Store at room temperature 58° - 86° F (15° - 30° C). Acoid storing product in direct sunlight •Protect product from excessive moisture

INACTIVE INGREDIENT

Inactive ingredients DIHYDROXYALUMINUM AMINOACETATE, GLYCERIN, KAOLIN, METHYLPARABEN, PROPYLPARABEN, PROPYLENE GLYCOL,

PVP, POLYACRYLIC ACID, POLYSORBATE 80, SODIUM POLYACRYLATE, TITANIUM DIOXIDE, TARTARIC ACID, WATER